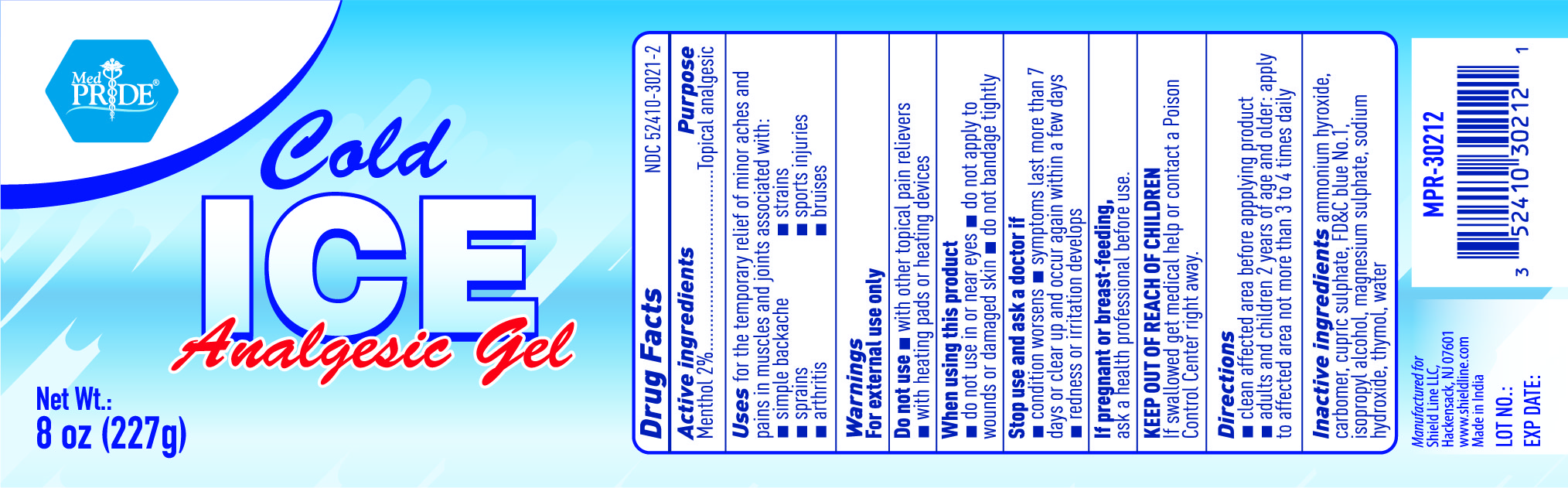 DRUG LABEL: MedPride Cold Ice Analgesic Gel
NDC: 52410-3021 | Form: GEL
Manufacturer: SHIELD LINE LLC
Category: otc | Type: HUMAN OTC DRUG LABEL
Date: 20250815

ACTIVE INGREDIENTS: MENTHOL 4.54 g/227 g
INACTIVE INGREDIENTS: CARBOXYPOLYMETHYLENE; CUPRIC SULFATE; THYMOL; FD&C BLUE NO. 1; WATER; SODIUM HYDROXIDE; AMMONIA; MAGNESIUM SULFATE, UNSPECIFIED; ISOPROPYL ALCOHOL

MedPride Cold Ice Gel

Active Ingredient

Menthol 2.0%

Purpose

Topical Analgesic

Uses:

- for temporary relief of minor aches and pains in muscles and joints associated with:
- simple backaches,
- strains
- sprains
- sports injuries
- arthritis
- bruises

Warnings

FOR EXTERNAL USE ONLY

Do not use:

- with other topical pain relievers
- with heating pads or heating devices

When using this product

- do not use in or near eyes
- do not apply to wounds or damaged skin
- do not bandage tightly

Stop use and ask a doctor if

- condition worsens
- symptoms last more than 7 days or clear up and occur again within a few days
- redness or irritation develops

If pregnant or breastfeeding

ask a health professional before use

KEEP OUT OF REACH OF CHILDREN

If swallowed get Medical Help or contact a Poison Control Center right away

Directions

- clean affected area before applying product
- adults and children 2 years of age and older; apply to affected area not more than 3 to 4 times daily

Inactive Ingredients

ammonium hydroxide, carbomer, cupric sulfate, FD&C Blue No. 1, isopropyl alcohol, magnesium sulfate, sodium hydroxide, thymol, water